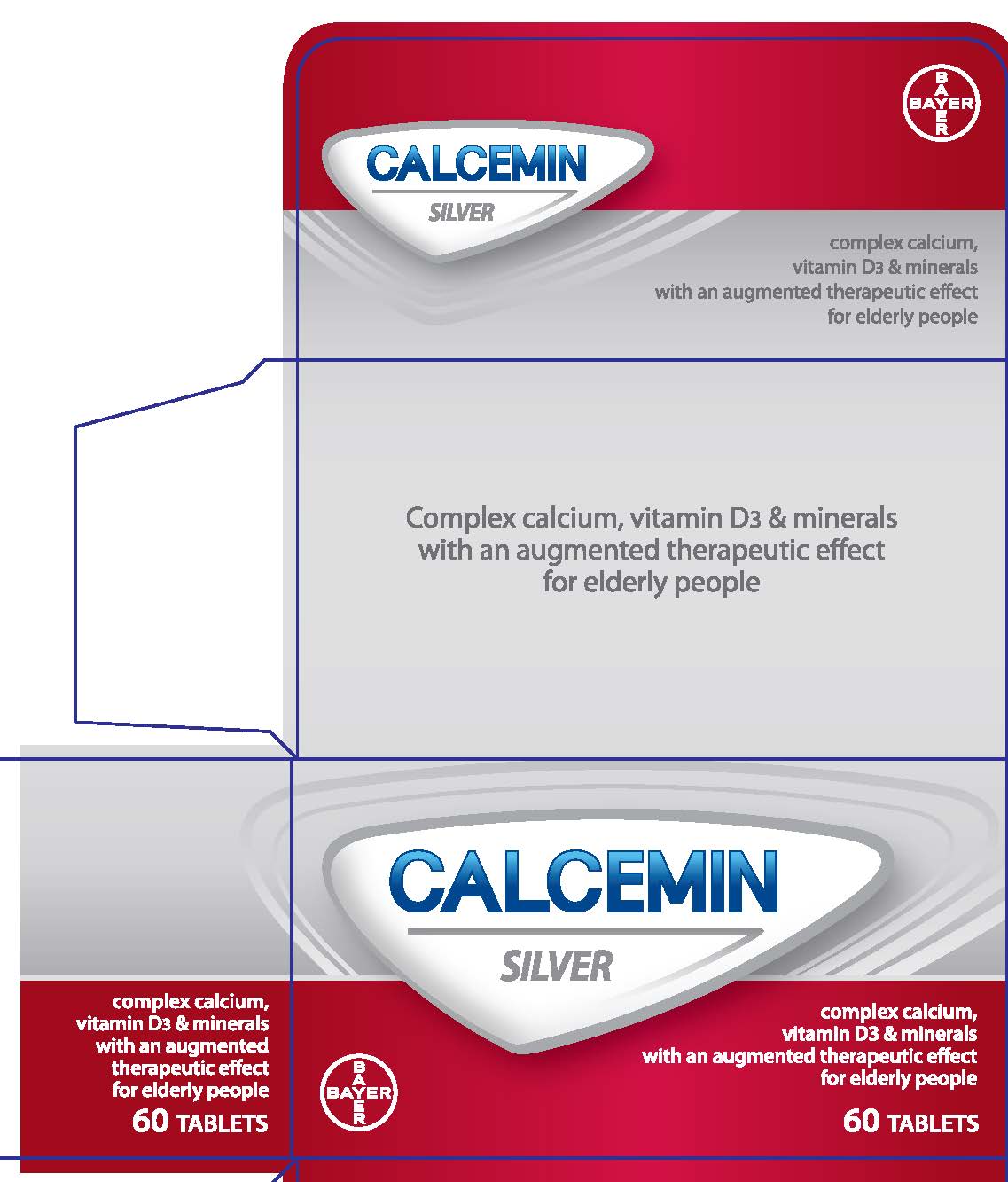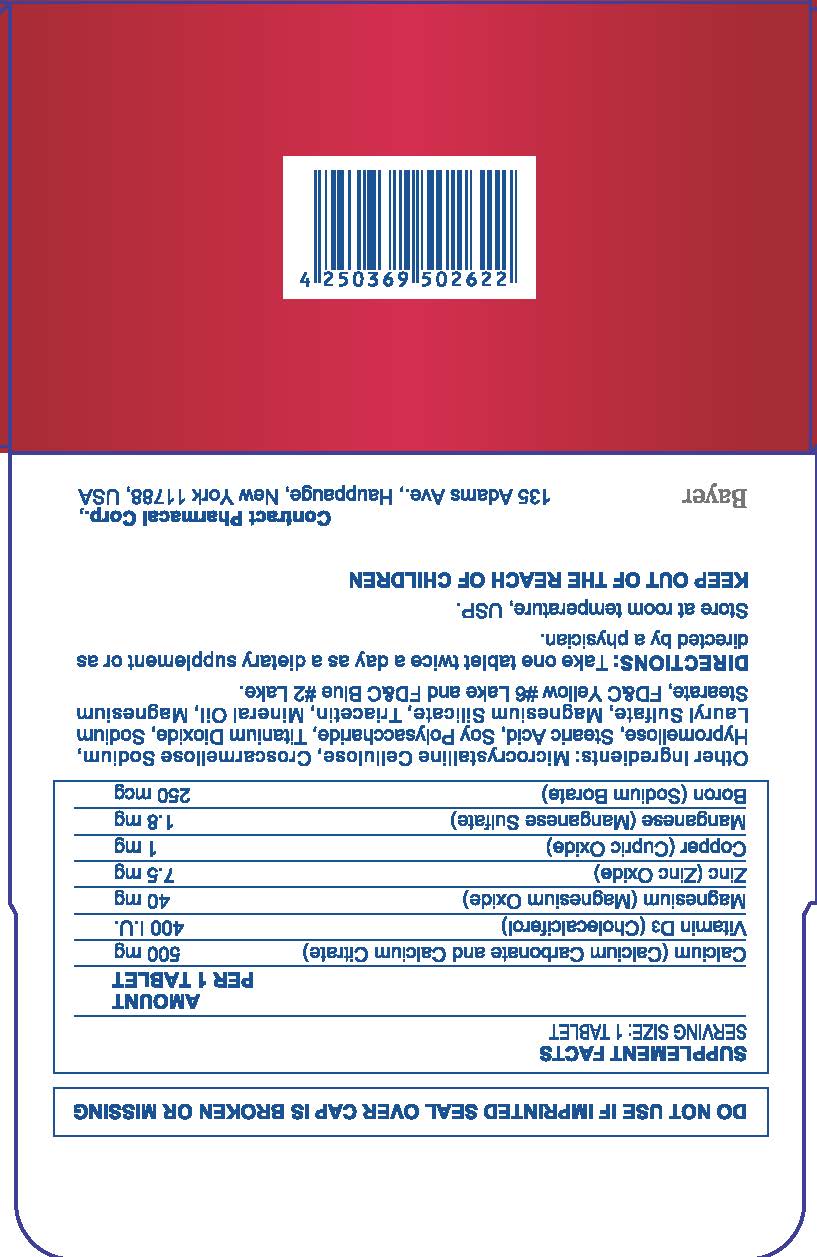 DRUG LABEL: Calcemin Silver
NDC: 0280-0273 | Form: TABLET, FILM COATED
Manufacturer: Bayer HealthCare LLC.
Category: otc | Type: HUMAN OTC DRUG LABEL
Date: 20210109

ACTIVE INGREDIENTS: BORON 2.6 mg/1 1; MAGNESIUM OXIDE 40 mg/1 1; ZINC OXIDE 7.5 mg/1 1
INACTIVE INGREDIENTS: SODIUM LAURYL SULFATE; MAGNESIUM STEARATE; TITANIUM DIOXIDE; HYPROMELLOSES; TRIACETIN; MINERAL OIL; FD&C BLUE NO. 2; FD&C YELLOW NO. 6; CROSCARMELLOSE; CELLULOSE, MICROCRYSTALLINE; MAGNESIUM SILICATE; WATER; STEARIC ACID

Calcemin Silver

Drug Facts